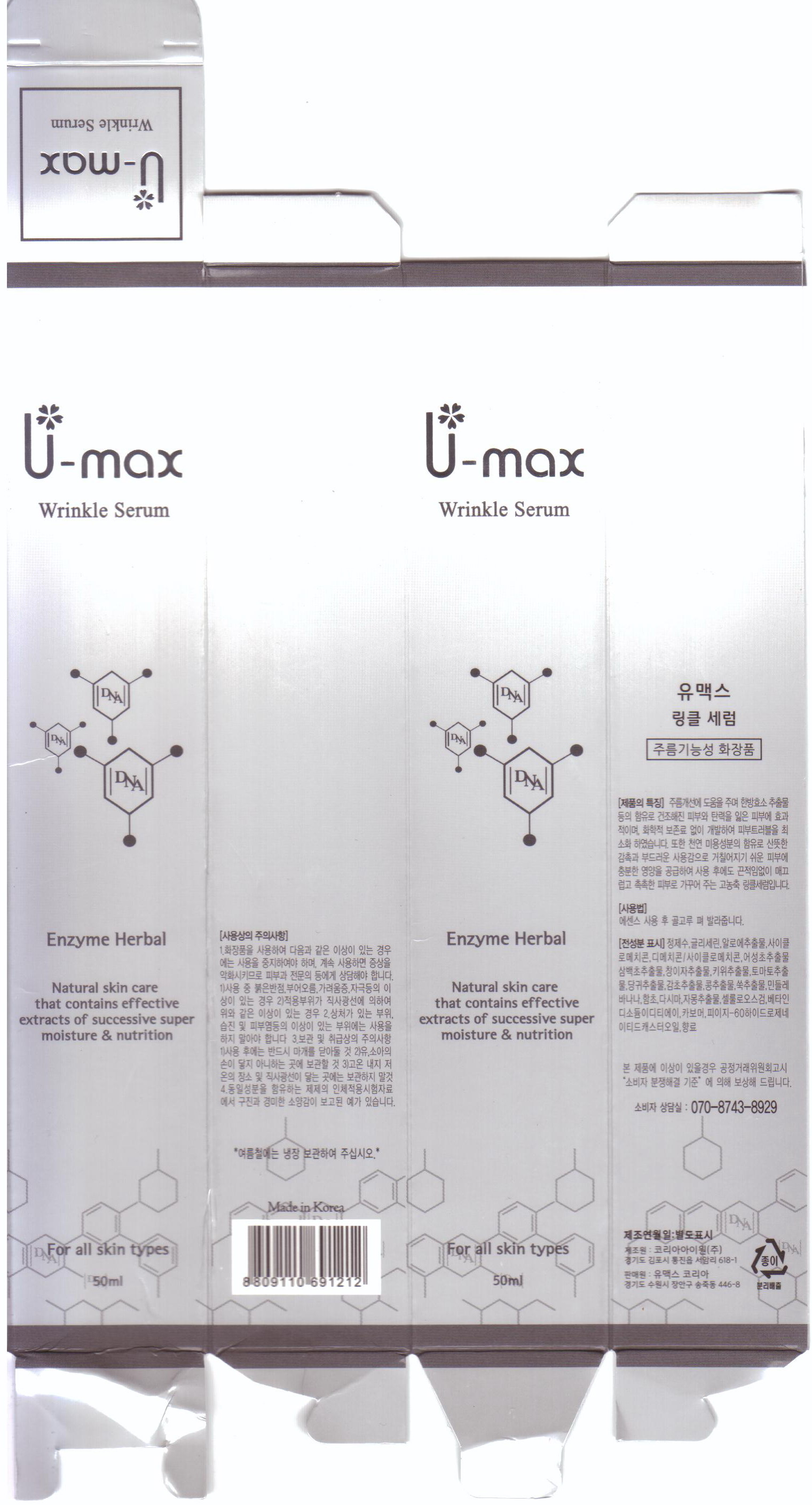 DRUG LABEL: U-max Wrinkle Serum
NDC: 50795-1001 | Form: LIQUID
Manufacturer: VS Shinbi Co., Ltd.
Category: otc | Type: HUMAN OTC DRUG LABEL
Date: 20120604

ACTIVE INGREDIENTS: ADENOSINE 0.04 mL/100 mL
INACTIVE INGREDIENTS: WATER; GLYCERIN; EDETATE DISODIUM; HOUTTUYNIA CORDATA FLOWERING TOP; XANTHIUM STRUMARIUM FRUIT; SOLANUM LYCOPERSICUM; ANGELICA GIGAS ROOT; GLYCYRRHIZA GLABRA; ARTEMISIA VULGARIS ROOT; KIWI FRUIT; BANANA; ALOE VERA LEAF; PURSLANE; SALICORNIA EUROPAEA; LAMINARIA JAPONICA; TARAXACUM OFFICINALE; CITRUS PARADISI SEED; BETAINE; POLYOXYL 60 HYDROGENATED CASTOR OIL; ALCOHOL; METHYLPARABEN; CYCLOMETHICONE

Drug Facts

active ingredient: adenosine

inactive ingredient: water, glycerin, disodium EDTA, carbomer, houttuynia cordata extract, xanthium strumarium fruit extract, angelica gigas root extract, glycyrrhiza glabra root extract, hydrolyzed soybean extract, artemisia vulgaris extract, actinidia chinensis fruit extract, musa sapientum fruit extract, aloe barbadensis leaf extract, perfurm, portulaca oleracea extract, salcornia herbacea extract, laminaria japonica extract, taraxacum officinale leaf extract, citrus paradisi seed oil, cellulose gum, betaine, peg-60 hydrogenated castor oil, triethanolamine, alcohol, methylparaben, cyclopentasioxane/dimethicone, cyclomethicone

PURPOSE

skin protectant (anti-wrinkle)

keep out of reach of the children

INDICATIONS AND USAGE

- apply only for skin
- apply 2 or 3 times a day with 5~6ml
- massage with your finger over 2 min and let them dry

WARNINGS

- keep out of eyes, ears and mouth
- if contact occurs, rinse away with plenty of cold water

DOSAGE AND ADMINISTRATION

- for external use only